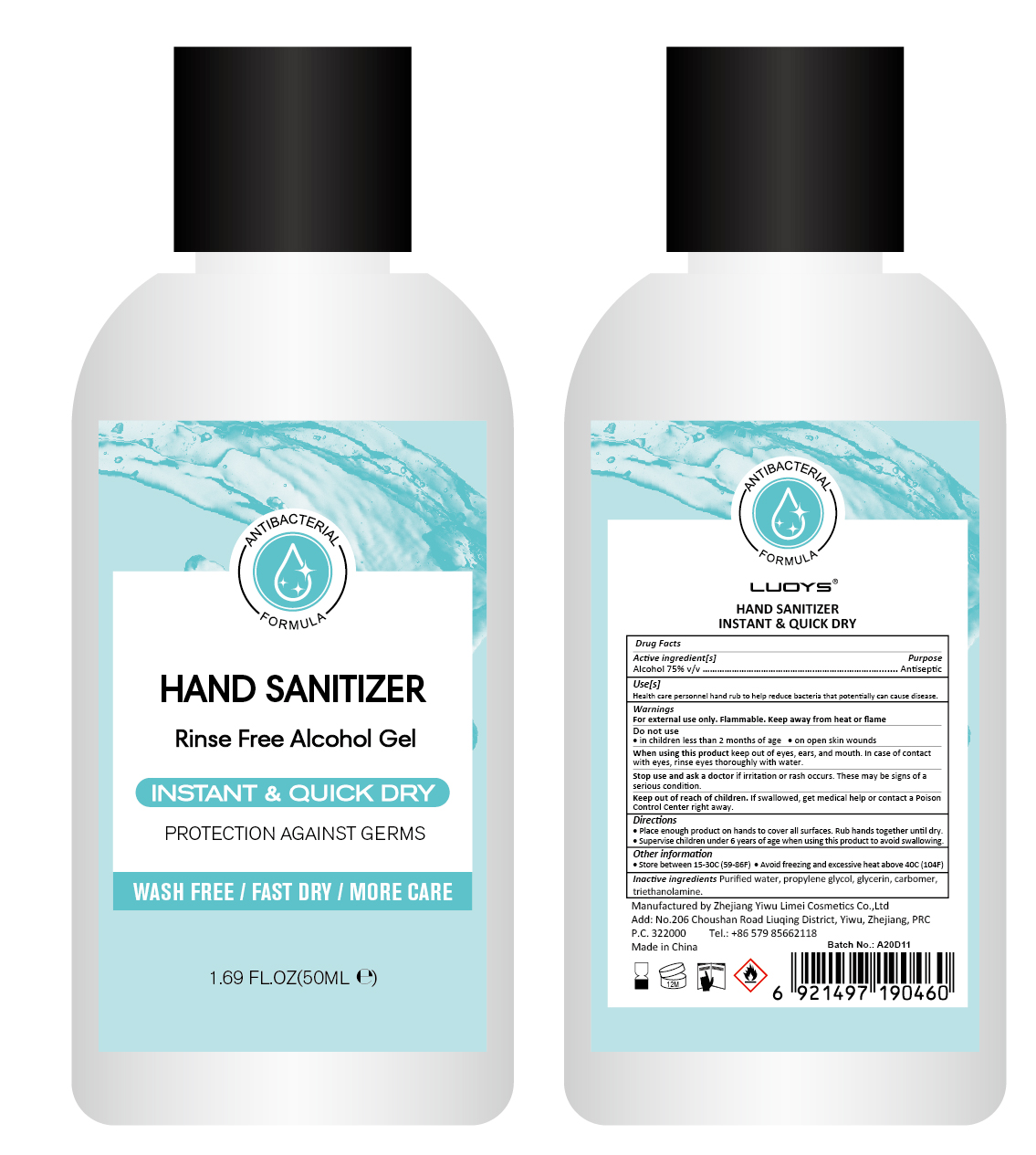 DRUG LABEL: LUOYS Hand Sanitizer
NDC: 74765-004 | Form: GEL
Manufacturer: ZheJiang Yiwu Limei Cosmetics Co., Ltd
Category: otc | Type: HUMAN OTC DRUG LABEL
Date: 20200426

ACTIVE INGREDIENTS: ALCOHOL 75 mL/100 mL
INACTIVE INGREDIENTS: CARBOMER 980; GLYCERIN; PROPYLENE GLYCOL; WATER; TROLAMINE

NA

Active Ingredient(s)

Alcohol 75% v/v. Purpose: Antiseptic

Purpose

Antiseptic, Hand Sanitizer

Use

Health care personnel hand rub to help reduce bacteria that potentially can cause disease

Warnings

For external use only. Flammable. Keep away from heat or flame

Do not use

- in children less than 2 months of age
- on open skin wounds

When using this product keep out of eyes, ears, and mouth. In case of contact with eyes, rinse eyes thoroughly with water.
Stop use and ask a doctor if irritation or rash occurs. These may be signs of a serious condition.
Keep out of reach of children. If swallowed, get medical help or contact a Poison Control Center right away.

Stop use and ask a doctor if irritation or rash occurs. These may be signs of a serious condition.

Keep out of reach of children. If swallowed, get medical help or contact a Poison Control Center right away.

Directions

- Place enough product on hands to cover all surfaces. Rub hands together until dry.
- Supervise children under 6 years of age when using this product to avoid swallowing.

Other information

- Store between 15-30C (59-86F)
- Avoid freezing and excessive heat above 40C (104F)

Inactive ingredients

purified water,glycerin, propylene glycol,carbomer,triethanolamine

Package Label - Principal Display Panel

29 mL NDC: 74765-004-01

50mL NDC: 74765-004-02

60 mL NDC: 74765-004-03

100 mL NDC: 74765-004-04

300 mL NDC: 74765-004-05

500 mL NDC: 74765-004-06

1000 mL NDC: 74765-004-07

2000 mL NDC: 74765-004-08

3000 mL NDC: 74765-004-09

5000 mL NDC: 74765-004-10

80 mL NDC: 74765-004-11

236mL NDC:74465-004-12